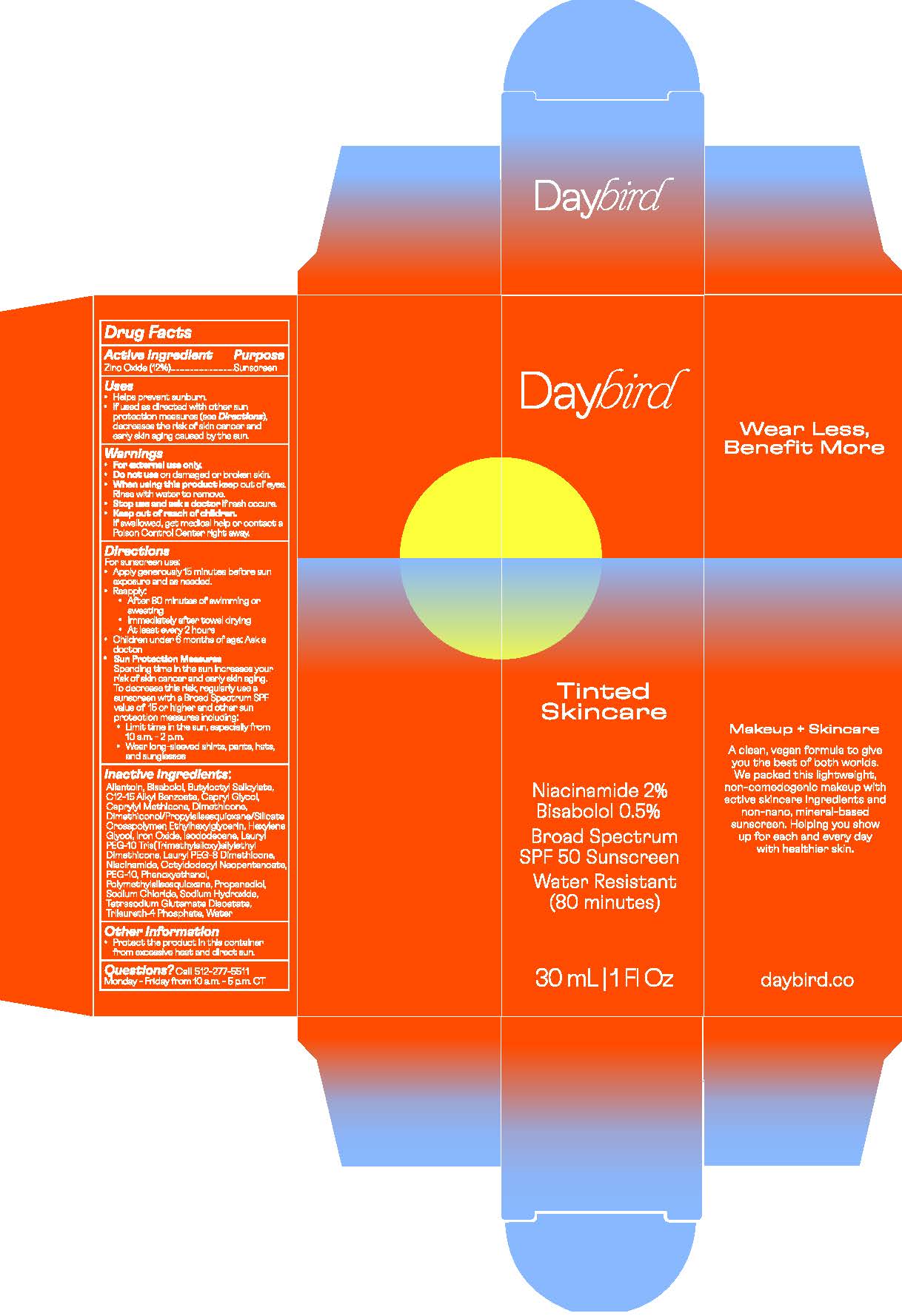 DRUG LABEL: Daybird Tinted Skincare (SHADE 1)
NDC: 82417-1062 | Form: LOTION
Manufacturer: Resette, Inc
Category: otc | Type: HUMAN OTC DRUG LABEL
Date: 20251009

ACTIVE INGREDIENTS: ZINC OXIDE 132 mg/1 mL
INACTIVE INGREDIENTS: SQUALANE; RUTIN; GLYCERIN; ISOSTEARIC ACID; FERRIC OXIDE YELLOW; POLYGLYCERYL-4 DIISOSTEARATE/POLYHYDROXYSTEARATE/SEBACATE; JOJOBA OIL; ORYZA SATIVA WHOLE; TRIDECYL SALICYLATE; SILICON DIOXIDE; TOCOPHEROL; CAPRYLYL GLYCOL; COCO-CAPRYLATE; NYLON-12; PHENYLPROPANOL; HELIANTHUS ANNUUS FLOWERING TOP; LECITHIN, SOYBEAN; METHYLHEPTYL ISOSTEARATE; METHYLPROPANEDIOL; POLYGLYCERYL-2 DIPOLYHYDROXYSTEARATE; ALLANTOIN; ALKYL (C12-15) BENZOATE; ROSMARINUS OFFICINALIS FLOWER; .ALPHA.-BISABOLOL, (+)-; SODIUM HYDROXIDE; WATER; NIACINAMIDE; PROPANEDIOL; TETRASODIUM GLUTAMATE DIACETATE; SODIUM CHLORIDE; HYDROGENATED SOYBEAN LECITHIN; FERRIC OXIDE RED; FERROSOFERRIC OXIDE

Daybird Tinted Skincare (SHADE 1)